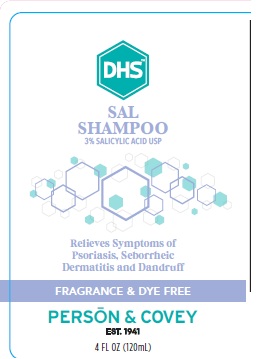 DRUG LABEL: DHS SAL
NDC: 0096-0738 | Form: SHAMPOO
Manufacturer: Person and Covey
Category: otc | Type: HUMAN OTC DRUG LABEL
Date: 20251128

ACTIVE INGREDIENTS: SALICYLIC ACID 0.035 g/1 g
INACTIVE INGREDIENTS: SODIUM C14-16 OLEFIN SULFONATE; WATER; TRIETHANOLAMINE LAURYL SULFATE; COCAMIDOPROPYL BETAINE; COCAMIDOPROPYL HYDROXYSULTAINE; PEG-8 DISTEARATE

DHS SAL

WARNINGS AND PRECAUTIONS

For external use only. Ask a physician before use if you have Psoriasis or Seborrheic Dermatitis that covers a large area of the body. Do not get into eyes. If contact occurs, rinse eyes thoroughly with water. Stop use and ask a physician if condition worsens or does not improve after regular use.

Dosage and Administration

Wet hair thoroughly. Apply a liberal amount of shampoo and massage into a rich lather. Allow lather to remain on scalp for several minutes. Rinse hair well and repeat application. For best results use at least twice a week or as directed by a physician. Store away from direct sunlight.

Indications and Use

Controls crusty, flaky buildup, while relieving scalp itching and flaking, symptomatic of Psoriasis and Seborrheic Dermatitis.

KEEP OUT OF REACH OF CHILDREN

If swallowed, get medical help or contact a Poison Control Center right away.

PURPOSE

Controls symptoms of Psoriasis, Seborrheic Dermatitis and Dandruff

INACTIVE INGREDIENTS

Purified Water

Sodium C14-16 Olefin Sulfonate

Triethanolamine Lauryl Sulfate

Cocamidopropyl Betaine

Cocamidopropyl Hydroxysultaine

PEG 8 Distearate

Active Ingredient

Salicylic Acid 35 mg/g